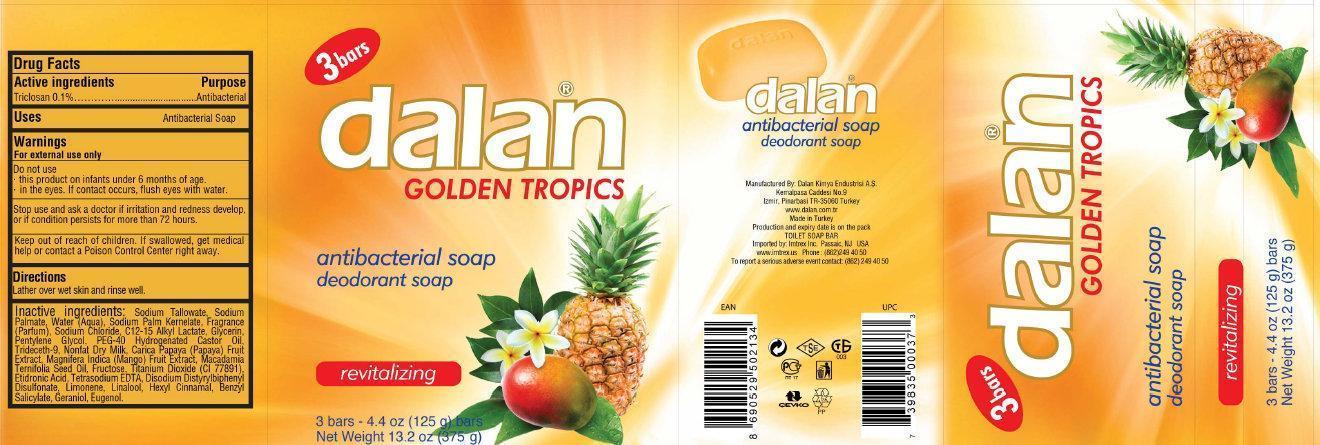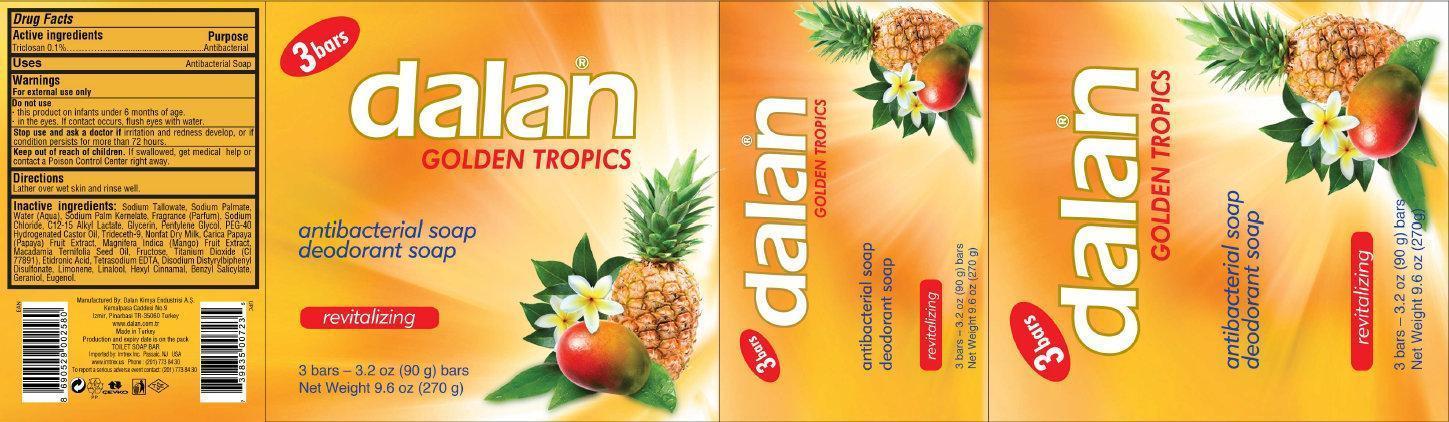 DRUG LABEL: dalan GOLDEN TROPICS antibacterial deodorant
                
NDC: 51209-002 | Form: SOAP
Manufacturer: Dalan Kimya Endustri A.S.
Category: otc | Type: HUMAN OTC DRUG LABEL
Date: 20150202

ACTIVE INGREDIENTS: TRICLOSAN 0.1 g/100 g
INACTIVE INGREDIENTS: SODIUM TALLOWATE, BEEF; SODIUM PALMATE; WATER; SODIUM PALM KERNELATE; SODIUM CHLORIDE; GLYCERIN; PENTYLENE GLYCOL; PEG-40 CASTOR OIL; TRIDECETH-9; SKIM MILK; PAPAYA; MANGO; MACADAMIA OIL; FRUCTOSE; COCO DIETHANOLAMIDE; EDETATE SODIUM; ETIDRONIC ACID; LIMONENE, (+)-; LINALOOL, (+)-; .ALPHA.-HEXYLCINNAMALDEHYDE; BENZYL SALICYLATE; GERANIOL; EUGENOL

dalan GOLDEN TROPICS antibacterial soap deodorant soap

Active Ingredient / Purpose

PURPOSE

Triclosan 0.1% ...... Antibacterial

Uses

Antibacterial Soap

Warnings

For external use only
Do not use

- this product on infants under 6 months of age.
- in the eyes. If contact occurs, flush eyes with water.

Stop use and ask a doctor if irritation and redness develops or if condition persists for more than 72 hours.

Keep out of reach of children. If swallowed, get medical help or contact a Poison Control Center right away.

Directions

Lather over wet skin and rinse well

Inactive Ingredients:

Sodium Tallowate, Sodium Palmate, Water (aqua), Sodium Palm Kernelate, Fragrance, Sodium Chloride, Alkyl Lactate, Glycerin, Pentylene Glycol, PEG-40 Hydrogenated Castor Oil, Trideceth-9. Nonfat Dry Milk, Carica Papaya (Papaya) Fruit Extract, Magnifera Indica (Mango) Fruit Extract, Macadamia Ternifolia Seed Oil, Fructose, Cocamide DEA, Tetrasodium EDTA, Etidronic Acid, Limonene, Linalool, Hexyl Cinnamal, Benzyl Salicylate, Geraniol, Eugenol